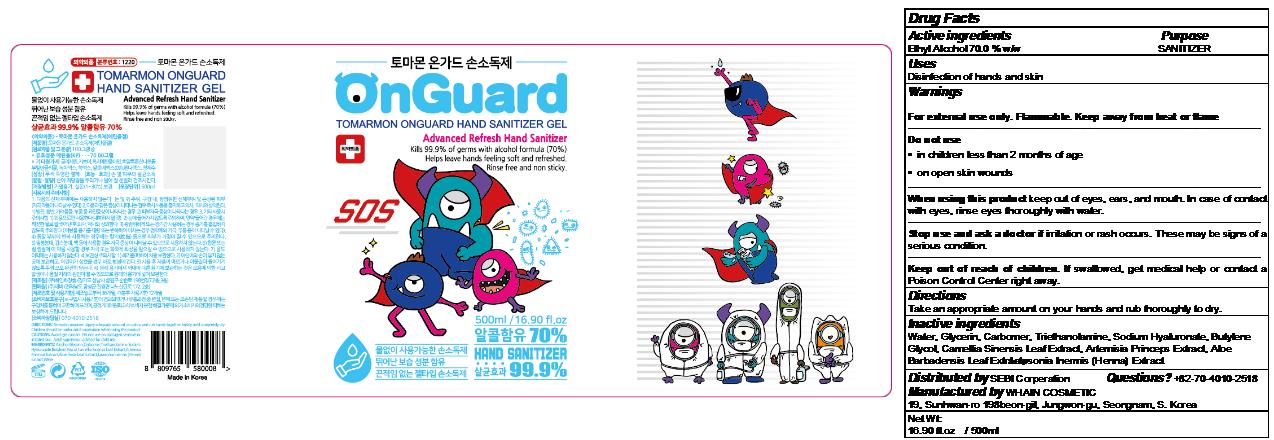 DRUG LABEL: TOMARMON ONGUARD HAND SANITIZER Gel
NDC: 73823-034 | Form: GEL
Manufacturer: WHAIN COSMETIC
Category: otc | Type: HUMAN OTC DRUG LABEL
Date: 20201215

ACTIVE INGREDIENTS: ALCOHOL 350 mL/500 mL
INACTIVE INGREDIENTS: BUTYLENE GLYCOL; WATER; ARTEMISIA PRINCEPS LEAF; GREEN TEA LEAF; CARBOMER HOMOPOLYMER, UNSPECIFIED TYPE; ALOE VERA LEAF; LAWSONIA INERMIS WHOLE; TROLAMINE; GLYCERIN; HYALURONATE SODIUM

[WHAIN COSMETIC] TOMARMON ONGUARD HAND SANITIZER GEL
500 mL